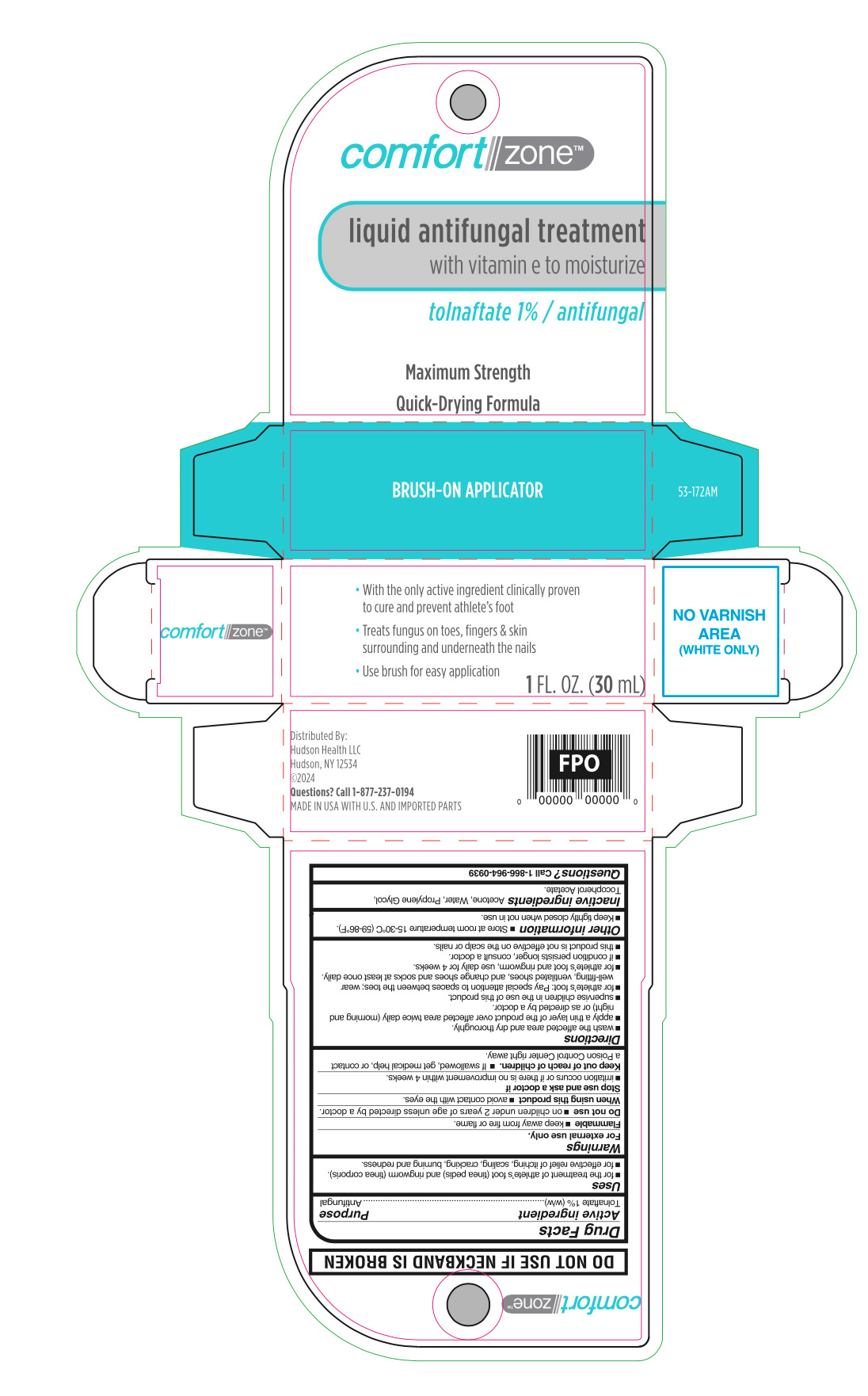 DRUG LABEL: Liquid Antifungal Treatment
NDC: 72446-012 | Form: LIQUID
Manufacturer: Hudson Health LLC
Category: otc | Type: HUMAN OTC DRUG LABEL
Date: 20251024

ACTIVE INGREDIENTS: TOLNAFTATE 10 mg/1 mL
INACTIVE INGREDIENTS: ACETONE; WATER; PROPYLENE GLYCOL; .ALPHA.-TOCOPHEROL ACETATE

Comfort Zone Liquid Antifungal Treatment

Active ingredient

Tolnaftate 1%

Purpose

Antifungal

Uses

for the treatment of athlete’s foot (tinea pedis) and ringworm (tinea corporis)

for effective relief of itching, scaling, cracking, burning and redness.

Warnings

For external use only.

Flammable

keep away from fire or flame.

Do not use

on children under 2 years of age unless directed by a doctor.

When using this product

avoid contact with the eyes.

Stop use and consult a doctor if

- irritation occurs or if there is no improvement within 4 weeks

Keep out of reach of children.

If swallowed, get medical help, or contact a Poison Control Center right away.

Directions

- wash the affected area and dry thoroughly.
- apply a thin layer of the product over affected area twice daily (morning and night) or as directed by a doctor.
- supervise children in the use of this product.
- for athlete’s foot: Pay special attention to spaces between the toes; wear well-fitting, ventilated shoes, and change shoes and socks at least once daily.
- for athlete’s foot and ringworm, use daily for 4 weeks.
- if condition persists longer, consult a doctor.
- this product is not effective on the scalp or nails.

Other information

- Store at room temperature 15°-30°C (59° - 86°F)
- Keep tightly closed when not in use

Inactive ingredient

Acetone, Water, Propylene Glycol, Tocopherol Acetate.

Questions?

Call 1-866-964-0939

Principal Display Panel

Comfort zone

liquid antifungal treatment

with vitamin e to moisturize

TOLNAFTATE 1%/ANTIFUNGAL

Maxiumum Strength

Brush- On Applicator

SHAKE WELL BEFORE USE

1 FL. OZ. (30 mL)